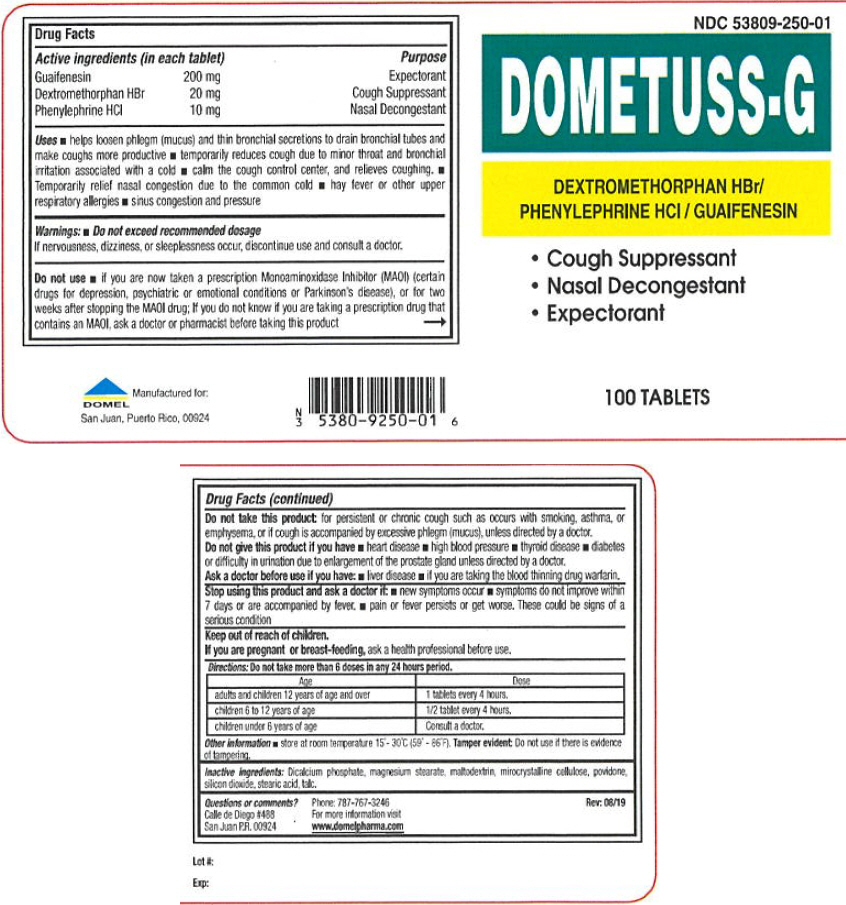 DRUG LABEL: DOMETUSS-G
NDC: 53809-250 | Form: TABLET
Manufacturer: DOMEL
Category: otc | Type: HUMAN OTC DRUG LABEL
Date: 20241206

ACTIVE INGREDIENTS: GUAIFENESIN 200 mg/1 1; DEXTROMETHORPHAN HYDROBROMIDE 20 mg/1 1; PHENYLEPHRINE HYDROCHLORIDE 10 mg/1 1
INACTIVE INGREDIENTS: ANHYDROUS DIBASIC CALCIUM PHOSPHATE; MAGNESIUM STEARATE; MALTODEXTRIN; MICROCRYSTALLINE CELLULOSE; POVIDONE, UNSPECIFIED; SILICON DIOXIDE; STEARIC ACID; TALC

DOMETUSS-G

Drug Facts

ACTIVE INGREDIENT

Active ingredients (in each tablet) |  | Purpose
Guaifenesin | 200 mg | Expectorant
Dextromethorphan HBr | 20 mg | Cough Suppressant
Phenylephrine HCl | 10 mg | Nasal Decongestant

Uses

- helps loosen phlegm (mucus) and thin bronchial secretions to drain bronchial tubes and make coughs more productive
- temporarily reduces cough due to minor throat and bronchial irritation associated with a cold
- calm the cough control center, and relieves coughing.
- Temporarily relief nasal congestion due to the common cold
- hay fever or other upper respiratory allergies
- sinus congestion and pressure

Warnings

- Do not exceed recommended dosage

If nervousness, dizziness, or sleeplessness occur, discontinue use and consult a doctor.

Do not use

- if you are now taken a prescription Monoaminoxidase Inhibitor (MAOI) (certain drugs for depression, psychiatric or emotional conditions or Parkinson's disease), or for two weeks after stopping the MAOI drug; If you do not know if you are taking a prescription drug that contains an MAOI, ask a doctor or pharmacist before taking this product

Do not take this product: for persistent or chronic cough such as occurs with smoking, asthma, or emphysema, or if cough is accompanied by excessive phlegm (mucus), unless directed by a doctor.

Do not give this product if you have

- heart disease
- high blood pressure
- thyroid disease
- diabetes or difficulty in urination due to enlargement of the prostate gland unless directed by a doctor.

Ask a doctor before use if you have

- liver disease
- if you are taking the blood thinning drug warfarin.

Stop using this product and ask a doctor if

- new symptoms occur
- symptoms do not improve within 7 days or are accompanied by fever.
- pain or fever persists or gets worse. These could be signs of a serious condition

Keep out of reach of children.

PREGNANCY OR BREAST FEEDING

If you are pregnant or breast-feeding, ask a health professional before use.

Directions

Do not take more than 6 doses in any 24 hours period.

Age | Dose
adults and children 12 years of age and over | 1 tablets every 4 hours.
children 6 to 12 years of age | 1/2 tablet every 4 hours.
children under 6 years of age | Consult a doctor.

Other information

- store at room temperature 15°- 30°C (59° - 86°F).

Tamper evident

Do not use if there is evidence of tampering.

Inactive ingredients

Dicalcium phosphate, magnesium stearate, maltodextrin, mirocrystalline cellulose, povidone, silicon dioxide, stearic acid, talc.

Questions or comments?

Calle de Diego #488
San Juan P.R. 00924

Phone: 787-767-3246
For more information visit
www.domelpharma.com

PRINCIPAL DISPLAY PANEL - 100 Tablet Bottle Label

NDC 53809-250-01

DOMETUSS-G

DEXTROMETHORPHAN HBr/
PHENYLEPHRINE HCl / GUAIFENESIN

- Cough Suppressant
- Nasal Decongestant
- Expectorant

100 TABLETS